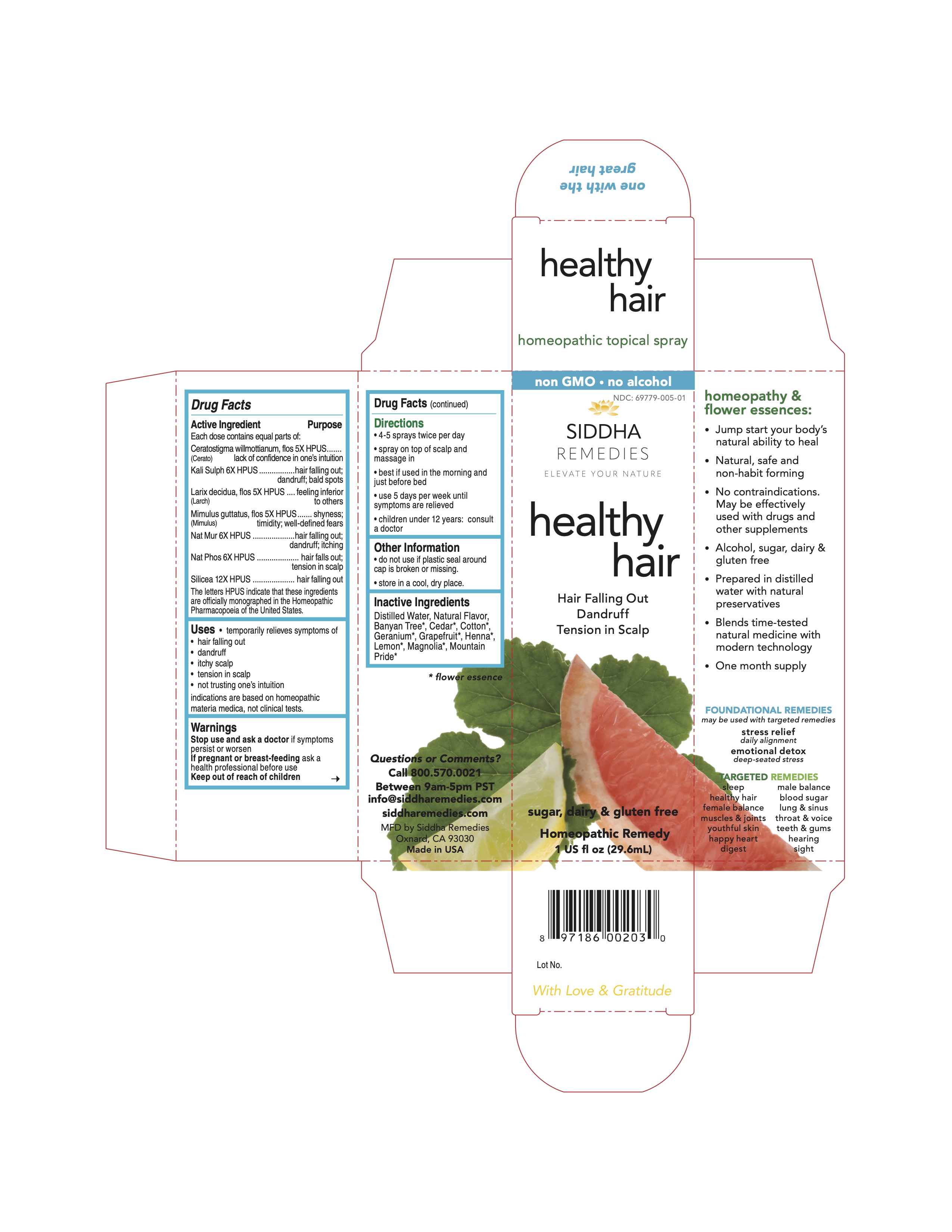 DRUG LABEL: healthy hair
NDC: 69779-005 | Form: SPRAY
Manufacturer: Siddha Flower Essences LLC
Category: homeopathic | Type: HUMAN OTC DRUG LABEL
Date: 20251231

ACTIVE INGREDIENTS: CERATOSTIGMA WILLMOTTIANUM FLOWER 5 [hp_X]/29.6 mL; POTASSIUM SULFATE 6 [hp_X]/29.6 mL; LARIX DECIDUA FLOWERING TOP 5 [hp_X]/29.6 mL; MIMULUS GUTTATUS FLOWERING TOP 5 [hp_X]/29.6 mL; SODIUM CHLORIDE 6 [hp_X]/29.6 mL; SODIUM PHOSPHATE, DIBASIC, HEPTAHYDRATE 6 [hp_X]/29.6 mL; SILICON DIOXIDE 12 [hp_X]/29.6 mL
INACTIVE INGREDIENTS: GRAPEFRUIT; LAWSONIA INERMIS FLOWERING TOP; LEMON; WATER

Drug Facts

Active Ingredient

Each dose contains equal parts of:
Ceratostigma willmottianum, flos (Cerato) 5X HPUS
Kali Sulph 6X HPUS
Larix decidua, flow (Larch) 5X HPUS
Mimulus guttatus, flos (Mimulus) 5X HPUS
Nat Mur 6X HPUS
Nat Phos 6X HPUS
Silicea 12X HPUS

Purpose

Each dose contains equal parts of:
Ceratostigma willmottianum, flos (Cerato) 5X HPUS...........lack of confidence in one's intuition
Kali Sulph 6X HPUS........................................................hair falling out; dandruff; bald spots
Larix decidua, flow (Larch) 5X HPUS.................................feeling inferior to others
Mimulus guttatus, flos (Mimulus) 5X HPUS.......................shyness; timidity; well-defined fears
Nat Mur 6X HPUS...........................................................hear falling out; dandruff; itching
Nat Phos 6X HPUS.........................................................hair falls out; tension in scalp
Silicea 12X HPUS...........................................................hair falling out

The letters HPUS indicate that these ingredients are officially monographed in the Homeopathic Pharmacopoeia of the United States.

Uses

- temporarily relieves symptoms of
- hair falling out
- dandruff
- itchy scalp
- tension in scalp
- not trusting one's intuition

indications are based on homeopathic materia medica, not clinical tests.

Warnings

Stop use and ask a doctor if symptoms persist or worsen

PREGNANCY OR BREAST FEEDING

If pregnant or breast-feeding ask a health professional before use

Keep out of reach of children

Directions

- 4-5 sprays twice per day
- spray on top of scalp and massage in
- best if used in the morning and just before bed
- use 5 days per week until symptoms are relieved
- children under 12 years: consult a doctor

Other Information

- do not use if plastic seal around cap is broken or missing.
- store in a cool, dry place.

Inactive Ingredients

Banyan Tree*, Cedar*, Cotton*, Geranium*, Grapefruit*, Henna*, Lemon* Magnolia*, Mountain Pride*, Natural Flavor, Purified Water

*flower essence

Questions or Comments?

Call 800.570.0021

Between 9am-5pm PST

siddhaflowers.com

info@siddhaflowers.com

MFD by Siddha Flower Essences
Oxnard, CA 93030

Made in USA

Side Panel

homeopathy and flower essences:

- Jump start your body's natural ability to heal
- Natural, safe, and non-habit forming
- No contraindications. May be effectively used with drugs and other supplements
- Alcohol, sugar, dairy and gluten free
- Prepared in purified water with natural preservatives
- Blends time-tested natural medicine with modern technology
- One month supply

FOUNDATIONAL REMEDIES
may be used with targeted remedies

stress relief
daily alignment
emotional detox
deep-seated stress

TARGETED REMEDIES

sleep male balance

healthy hair blood sugar

female balance lung and sinus

muscles and joints throat and voice

youthful skin teeth and gums

healthy heart hearing

digest sight

Principal Display Panel

non GMO - no alcohol
siddha cell salts + flower essences
healthy hair
Hair Falling Out
Dandruff
Tension in Scalp
sugar, dairy and gluten free
Homeopathic Remedy
1 US fl oz (29.6mL)